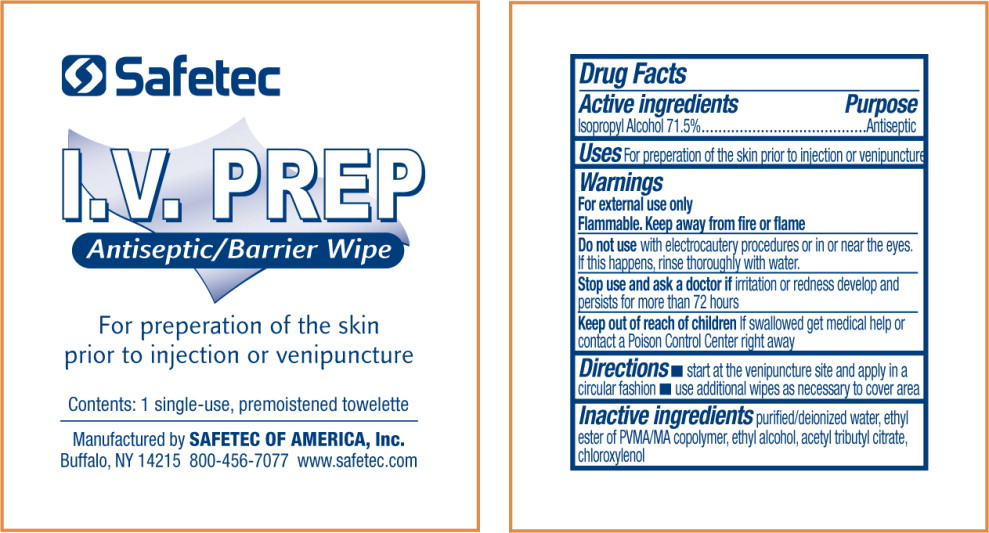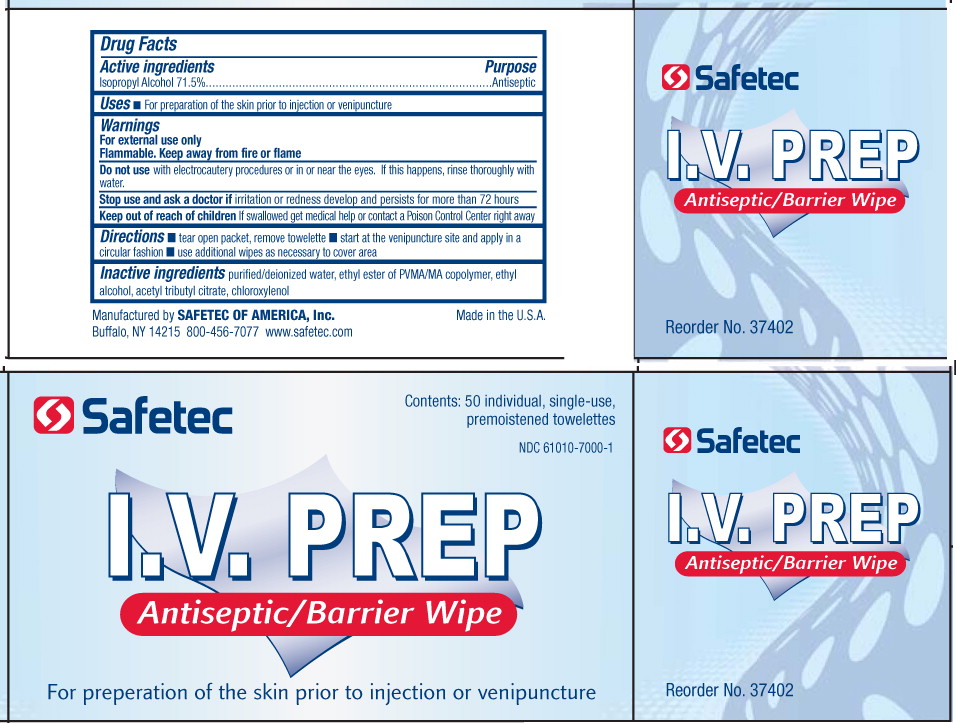 DRUG LABEL: Antiseptic
NDC: 61010-7000 | Form: LIQUID
Manufacturer: Safetec of America
Category: otc | Type: HUMAN OTC DRUG LABEL
Date: 20110609

ACTIVE INGREDIENTS: isopropyl alcohol 715 mL/1 L
INACTIVE INGREDIENTS: water; alcohol; acetyltributyl citrate; chloroxylenol

Drug Facts

Active Ingredients

Isopropyl Alcohol 71.5%

Purpose

Antiseptic

Uses

- For preparation of the skin prior to injection or venipuncture

Warnings

For external use only

Flammable. Keep away from fire or flame

Do not use with electrocautery procedures or in or near the eyes. If this happens, rinse thoroughly with water.

Stop use and ask doctor if irritation or redness develop and persists for more than 72 hours

Keep out of reach of children If swallowed get medical help or contact a Poison Control Center right away

Directions

- start at the venipuncture site and apply in a circular fashion
- use additional wipes as necessary to cover area

Inactive ingredients

purified/deionized water, ethyl ester of PVMA/MA copolymer, ethyl alcohol, acetyl tributyl citrate, chloroxylenol

PRINCIPAL DISPLAY PANEL – packet label

Safetec

I.V. Prep

Antiseptic/Barrier Wipe
For preparation of the skin prior to injection or venipuncture

Contents: 1 single-use, premoistened towelette

Manufactured by SAFETEC OF AMERICA, Inc.
Buffalo, NY 14215 800-456-7077 www.safetec.com

PRINCIPAL DISPLAY PANEL – box

Safetec

Contents: 50 individual, single-use, premoistened towelettes

NDC 61010-7000-1

I.V. Prep

Antiseptic/Barrier Wipe

For preparation of the skin prior to injection or venipuncture